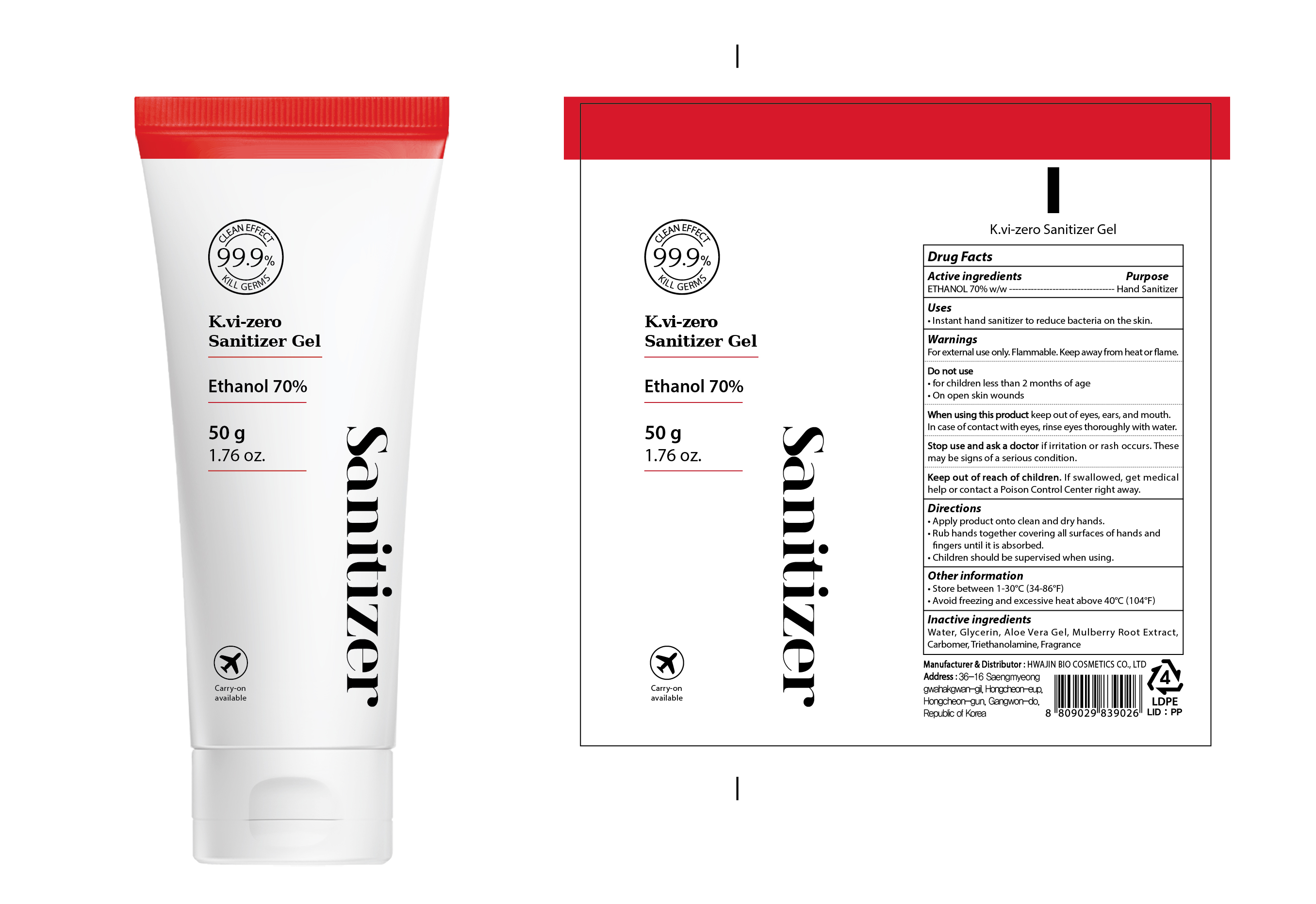 DRUG LABEL: K.vi zero Sanitizer
NDC: 78394-030 | Form: GEL
Manufacturer: HWAJIN BIO COSMETICS CO., LTD.
Category: otc | Type: HUMAN OTC DRUG LABEL
Date: 20200619

ACTIVE INGREDIENTS: ALCOHOL 35 g/50 g
INACTIVE INGREDIENTS: Water; Glycerin; ALOE VERA LEAF; MORUS ALBA ROOT; CARBOMER HOMOPOLYMER, UNSPECIFIED TYPE; TROLAMINE

ACTIVE INGREDIENT

ETHANOL 70% w/w

INACTIVE INGREDIENTS

Water, Glycerin, Aloe Vera Gel, Mulberry Root Extract, Carbomer, Triethanolamine, Fragrance

PURPOSE

Hand Sanitizer

WARNINGS

For external use only. Flammable. Keep away from heat or flame.
--------------------------------------------------------------------------------------------------------
Do not use
• In children less than 2 months of age
• On open skin wounds
--------------------------------------------------------------------------------------------------------
When using this product keep out of eyes, ears, and mouth. In case of contact with eyes, rinse eyes thoroughly with water.
--------------------------------------------------------------------------------------------------------
Stop use and ask a doctor if irritation or rash occurs. These may be signs of a serious condition.

KEEP OUT OF REACH OF CHILDREN

If swallowed, get medical help or contact a Poison Control Center right away.

Uses

Instant hand sanitizer to reduce bacteria on the skin.

Directions

• Apply product onto clean and dry hands.
• Rub hands together covering all surfaces of hands and fingers until it is absorbed.
• Children should be supervised when using.

Other information

• Store between 1-30°C (34-86°F)
• Avoid freezing and excessive heat above 40°C (104°F)